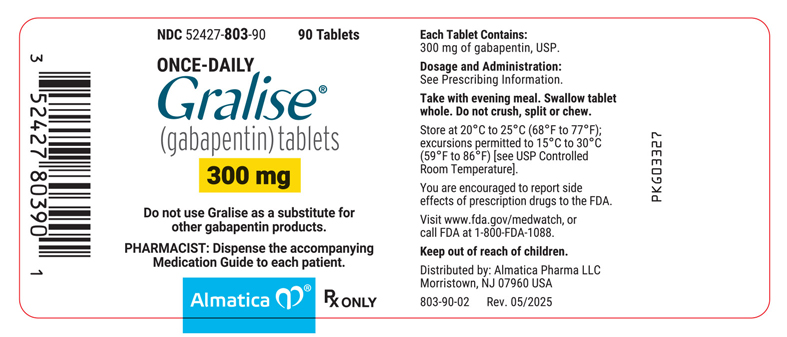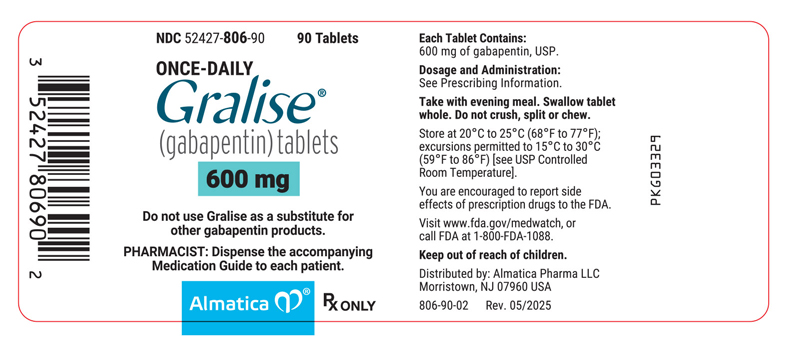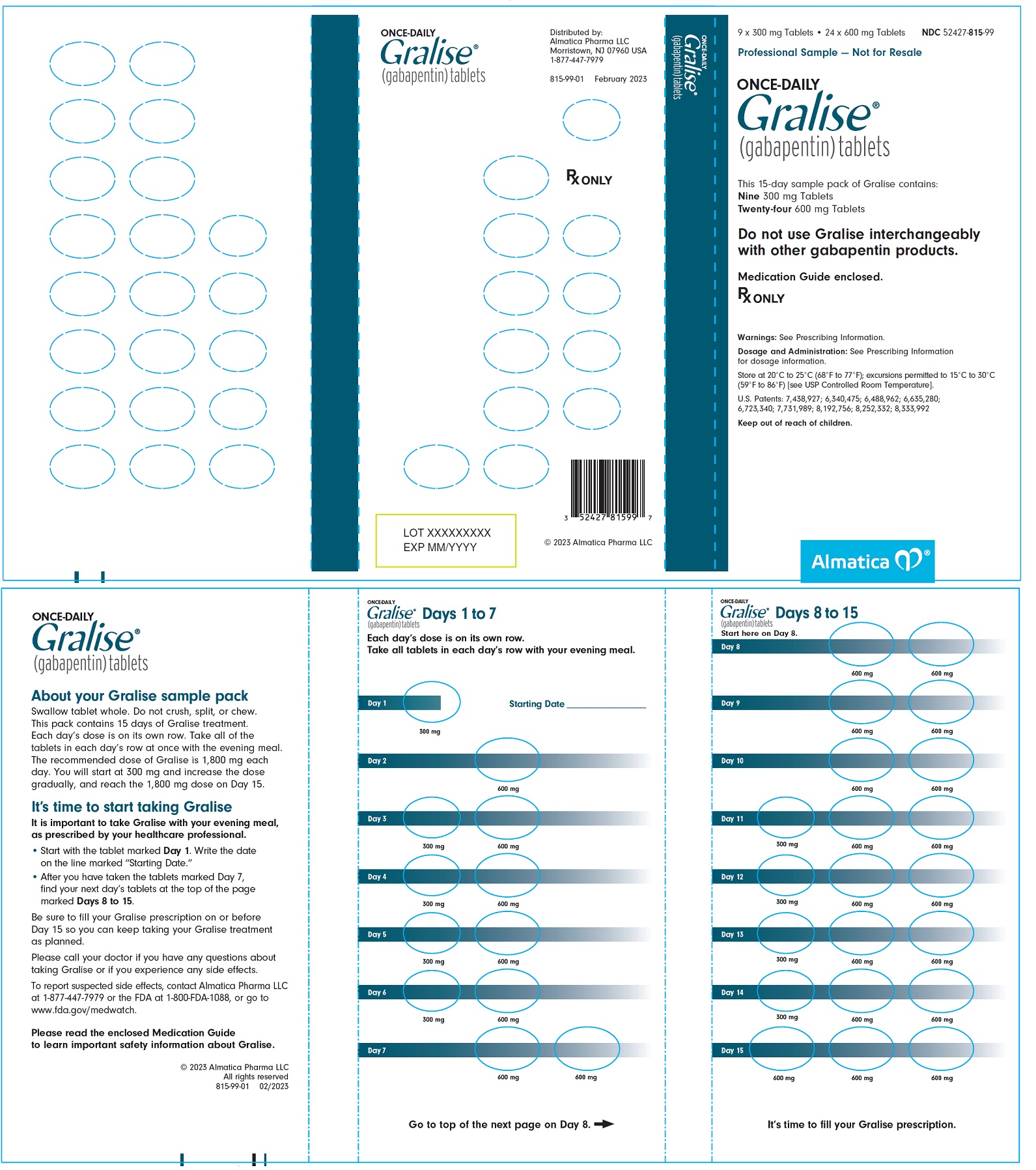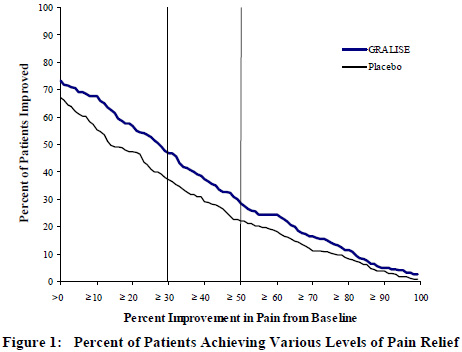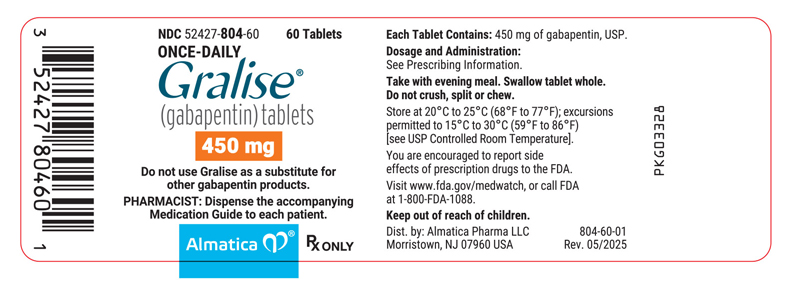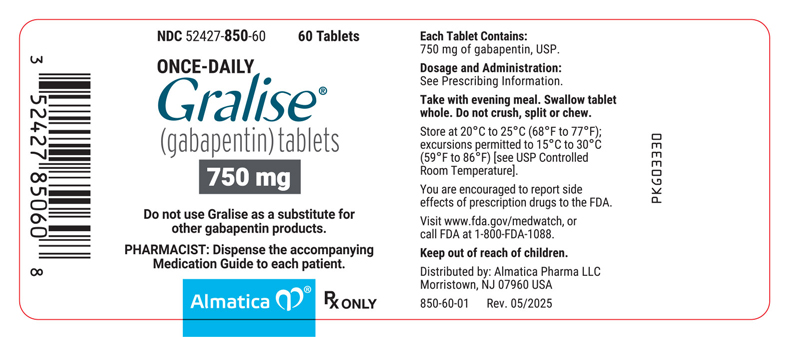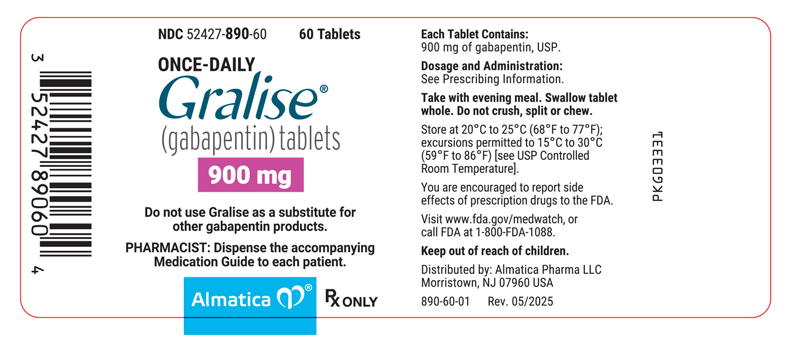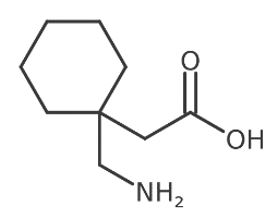 DRUG LABEL: Gralise
NDC: 52427-803 | Form: TABLET, FILM COATED
Manufacturer: Almatica Pharma LLC
Category: prescription | Type: HUMAN PRESCRIPTION DRUG LABEL
Date: 20250501

ACTIVE INGREDIENTS: GABAPENTIN 300 mg/1 1
INACTIVE INGREDIENTS: COPOVIDONE K25-31; HYPROMELLOSE, UNSPECIFIED; MAGNESIUM STEARATE; MICROCRYSTALLINE CELLULOSE; POLYETHYLENE GLYCOL, UNSPECIFIED; POLYVINYL ALCOHOL, UNSPECIFIED; TITANIUM DIOXIDE; TALC; POLYETHYLENE GLYCOL 3350; LECITHIN, SOYBEAN

HIGHLIGHTS OF PRESCRIBING INFORMATION

These highlights do not include all the information needed to use GRALISE safely and effectively. See full prescribing information for GRALISE.
GRALISE® (gabapentin) tablets, for oral use
Initial U.S. Approval: 1993

RECENT MAJOR CHANGES

Warnings and Precautions (5.1, 5.2) | 04/2025

1 INDICATIONS AND USAGE

GRALISE is indicated for the management of Postherpetic Neuralgia (PHN).

Important Limitation: GRALISE is not substitutable with other gabapentin products because of differing pharmacokinetic profiles that affect the frequency of administration (See Warnings and Precautions)

2 DOSAGE AND ADMINISTRATION

- GRALISE should be titrated to an 1,800 mg dose taken orally, once-daily, with the evening meal. GRALISE tablets should be swallowed whole. Do not crush, split, or chew the tablets. (2.1)
- If GRALISE dose is reduced, discontinued, or substituted with an alternative medication, this should be done gradually over a minimum of 1 week or longer (at the discretion of the prescriber). (2.1)
- Renal impairment: Dose should be adjusted in patients with reduced renal function. GRALISE should not be used in patients with CrCl less than 30 or in patients on hemodialysis. (2.2)

3 DOSAGE FORMS AND STRENGTHS

- Tablets: 300 mg, 450 mg, 600 mg, 750 mg, and 900 mg (3)

4 CONTRAINDICATIONS

GRALISE is contraindicated in patients who have demonstrated hypersensitivity to the drug or its ingredients. (4)

5 WARNINGS AND PRECAUTIONS

- GRALISE is not substitutable with other gabapentin products
- Antiepileptic drugs, including gabapentin, the active ingredient in GRALISE, increase the risk of suicidal thoughts or behavior (5.1)
- Abrupt or rapid discontinuation may increase the risk for seizures. Withdrawal symptoms or suicidal behavior and ideation have been observed after discontinuation. Taper GRALISE gradually over a minimum of 1 week. (5.2)
- Respiratory depression may occur with GRALISE when used with concomitant CNS depressants or in the setting of underlying respiratory impairment. Monitor patients and adjust dosage as appropriate. (5.3)

6 ADVERSE REACTIONS

- The most common adverse reaction (greater than or equal to 5% and twice placebo) is dizziness. (6.1)

To report SUSPECTED ADVERSE REACTIONS, contact Almatica Pharma LLC at 1-877-447-7979 or FDA at 1-800-FDA-1088 or www.fda.gov/medwatch

7 DRUG INTERACTIONS

- An increase in gabapentin AUC values have been reported when administered with hydrocodone. (7.6)
- An increase in gabapentin AUC values have been reported when administered with morphine. (7.7)
- An antacid containing aluminum hydroxide and magnesium hydroxide reduced the bioavailability of gabapentin immediate release by about approximately 20%, but by only 5% when gabapentin was taken 2 hours after antacids. It is recommended that GRALISE be taken at least 2 hours following antacid administration. (7.10)

8 USE IN SPECIFIC POPULATIONS

- Elderly: Reductions in GRALISE dose should be made in patients with age-related compromised renal function. (8.5)
- Renal impairment: Dosage adjustment is necessary for patients with impaired renal function. (8.7)

FULL PRESCRIBING INFORMATION

1 INDICATIONS AND USAGE

GRALISE is indicated for the management of postherpetic neuralgia.

GRALISE is not substitutable with other gabapentin products because of differing pharmacokinetic profiles that affect the frequency of administration.

2 DOSAGE AND ADMINISTRATION

2.1 Postherpetic Neuralgia

Do not use GRALISE as a substitute for other gabapentin products.

Titrate GRALISE to an 1,800 mg dose taken orally once daily with the evening meal. GRALISE tablets should be swallowed whole. Do not split, crush, or chew the tablets.

If GRALISE dosing is reduced, discontinued, or substituted with an alternative medication, this should be done gradually over a minimum of one week or longer (at the discretion of the prescriber).

In adults with postherpetic neuralgia, GRALISE therapy should be initiated and titrated as follows:

Table 1: GRALISE Recommended Titration Schedule
 | Day 1 | Day 2 | Days 3-6 | Days 7-10 | Days 11-14 | Day 15
Daily Dose | 300 mg | 600 mg | 900 mg | 1,200 mg | 1,500 mg | 1,800 mg

2.2 Patients with Renal Impairment

In patients with stable renal function, creatinine clearance (CCr) can be reasonably well estimated using the equation of Cockcroft and Gault:
For females CCr=(0.85)(140-age)(weight)/[(72)(SCr)]
For males CCr=(140-age)(weight)/[(72)(SCr)]
where age is in years, weight is in kilograms and SCr is serum creatinine in mg/dL.

The dose of GRALISE should be adjusted in patients with reduced renal function, according to Table 2. Patients with reduced renal function must initiate GRALISE at a daily dose of 300 mg. GRALISE should be titrated following the schedule outlined in Table 1. Daily dosing in patients with reduced renal function must be individualized based on tolerability and desired clinical benefit.

Table 2: GRALISE Dosage Based on Renal Function
Once-daily dosing
Creatinine Clearance (mL/min) | GRALISE Dose (once daily with evening meal)
≥ 60 | 1,800 mg
30 - 60 | 600 mg to 1,800 mg
< 30 | GRALISE should not be administered
patients receiving hemodialysis | GRALISE should not be administered

3 DOSAGE FORMS AND STRENGTHS

Tablets:

- 300 mg, white, oval, debossed with “SLV” on one side and “300” on the other side.
- 450 mg, red, oval, debossed with “ALM” on one side and “450” on the other side.
- 600 mg, beige, oval, debossed with “SLV” on one side and “600” on the other side.
- 750 mg, yellow, oval, debossed with “ALM” on one side and “750” on the other side.
- 900 mg, pink, oval, debossed with “ALM” on one side and “900” on the other side.

4 CONTRAINDICATIONS

GRALISE is contraindicated in patients with demonstrated hypersensitivity to the drug or its ingredients.

5 WARNINGS AND PRECAUTIONS

GRALISE is not substitutable with other gabapentin products because of differing pharmacokinetic profiles that affect the frequency of administration.

The safety and effectiveness of GRALISE in patients with epilepsy has not been studied.

5.1 Suicidal Behavior and Ideation

Antiepileptic drugs (AEDs), including gabapentin, the active ingredient in GRALISE, increase the risk of suicidal thoughts or behavior in patients taking these drugs for any indication. Suicidal behavior and ideation have also been reported in patients after discontinuation of gabapentin [see Warnings and Precautions (5.3)]. Patients treated with any AED for any indication should be monitored for the emergence or worsening of depression, suicidal thoughts or behavior, and/or any unusual changes in mood or behavior.

Pooled analyses of 199 placebo-controlled clinical trials (mono- and adjunctive therapy) of 11 different AEDs showed that patients randomized to one of the AEDs had approximately twice the risk (adjusted Relative Risk 1.8, 95% CI:1.2, 2.7) of suicidal thinking or behavior compared to patients randomized to placebo. In these trials, which had a median treatment duration of 12 weeks, the estimated incidence rate of suicidal behavior or ideation among 27,863 AED-treated patients was 0.43%, compared to 0.24% among 16,029 placebo-treated patients, representing an increase of approximately one case of suicidal thinking or behavior for every 530 patients treated. There were four suicides in drug-treated patients in the trials and none in placebo-treated patients, but the number is too small to allow any conclusion about drug effect on suicide.

The increased risk of suicidal thoughts or behavior with AEDs was observed as early as one week after starting drug treatment with AEDs and persisted for the duration of treatment assessed. Because most trials included in the analysis did not extend beyond 24 weeks, the risk of suicidal thoughts or behavior beyond 24 weeks could not be assessed.

The risk of suicidal thoughts or behavior was generally consistent among drugs in the data analyzed. The finding of increased risk with AEDs of varying mechanisms of action and across a range of indications suggests that the risk applies to all AEDs used for any indication. The risk did not vary substantially by age (5-100 years) in the clinical trials analyzed. Table 3 shows absolute and relative risk by indication for all evaluated AEDs.

Table 3: Risk by Indication for Antiepileptic Drugs (including gabapentin, the active ingredient in GRALISE) in the Pooled Analysis
Indication | Placebo Patients with Events Per 1,000 Patients | Drug Patients with Events Per 1,000 Patients | Relative Risk: Incidence of Events in Drug Patients/Incidence in Placebo Patients | Risk Difference: Additional Drug Patients with Events Per 1,000 Patients
Epilepsy | 1.0 | 3.4 | 3.5 | 2.4
Psychiatric | 5.7 | 8.5 | 1.5 | 2.9
Other | 1.0 | 1.8 | 1.9 | 0.9
Total | 2.4 | 4.3 | 1.8 | 1.9

The relative risk for suicidal thoughts or behavior was higher in clinical trials for epilepsy than in clinical trials for psychiatric or other conditions, but the absolute risk differences were similar for the epilepsy and psychiatric indications.

Anyone considering prescribing GRALISE must balance the risk of suicidal thoughts or behavior with the risk of untreated illness. Epilepsy and many other illnesses for which products containing active components that are AEDs (such as gabapentin, the active component in GRALISE) are prescribed are themselves associated with morbidity and mortality and an increased risk of suicidal thoughts and behavior. Should suicidal thoughts and behavior emerge during treatment, the prescriber needs to consider whether the emergence of these symptoms in any given patient may be related to the illness being treated.

Patients, their caregivers, and families should be informed that GRALISE contains gabapentin which is also used to treat epilepsy and that AEDs increase the risk of suicidal thoughts and behavior and should be advised of the need to be alert for the emergence or worsening of the signs and symptoms of depression, any unusual changes in mood or behavior, or the emergence of suicidal thoughts, behavior, or thoughts about self-harm. Behaviors of concern should be reported immediately to healthcare providers.

5.2 Increased Risk of Adverse Reactions with Abrupt or Rapid Discontinuation

After discontinuation of short-term and long-term treatment with gabapentin, withdrawal symptoms have been observed in some patients [see Adverse Reactions (6.2) and Drug Abuse and Dependence (9.3)]. Suicidal behavior and ideation have also been reported in patients after discontinuation of gabapentin [see Warnings and Precautions (5.1)]. If GRALISE is discontinued, this should be done gradually over a minimum of 1 week or longer (at the discretion of the prescriber).

5.3 Respiratory Depression

There is evidence from case reports, human studies, and animal studies associating gabapentin with serious, life-threatening, or fatal respiratory depression when co-administrated with central nervous system (CNS) depressants, including opioids, or in the setting of underlying respiratory impairment. When the decision is made to co-prescribe GRALISE with another CNS depressant, particularly an opioid, or to prescribe GRALISE to patients with underlying respiratory impairment, monitor patients for symptoms of respiratory depression and sedation, and consider initiating GRALISE at a low dose. The management of respiratory depression may include close observation, supportive measures, and reduction or withdrawal of CNS depressants (including GRALISE).

5.4 Tumorigenic Potential

In standard preclinical in vivo lifetime carcinogenicity studies, an unexpectedly high incidence of pancreatic acinar adenocarcinomas was identified in male, but not female, rats. The clinical significance of this finding is unknown.

In clinical trials of gabapentin therapy in epilepsy comprising 2,085 patient-years of exposure in patients over 12 years of age, new tumors were reported in 10 patients, and pre-existing tumors worsened in 11 patients, during or within 2 years after discontinuing the drug. However, no similar patient population untreated with gabapentin was available to provide background tumor incidence and recurrence information for comparison. Therefore, the effect of gabapentin therapy on the incidence of new tumors in humans or on the worsening or recurrence of previously diagnosed tumors is unknown.

5.5 Drug Reaction with Eosinophilia and Systemic Symptoms (DRESS)/Multiorgan Hypersensitivity

Drug Reaction with Eosinophilia and Systemic Symptoms (DRESS), also known as Multiorgan Hypersensitivity, has been reported in patients taking antiepileptic drugs, including GRALISE. Some of these events have been fatal or life-threatening. DRESS typically, although not exclusively, presents with fever, rash, and/or lymphadenopathy in association with other organ system involvement, such as hepatitis, nephritis, hematological abnormalities, myocarditis, or myositis sometimes resembling an acute viral infection. Eosinophilia is often present. Because this disorder is variable in its expression, other organ systems not noted here may be involved.

It is important to note that early manifestations of hypersensitivity, such as fever or lymphadenopathy, may be present even though rash is not evident. If such signs or symptoms are present, the patient should be evaluated immediately. GRALISE should be discontinued if an alternative etiology for the signs or symptoms cannot be established.

5.6 Laboratory Tests

Clinical trial data do not indicate that routine monitoring of clinical laboratory procedures is necessary for the safe use of GRALISE. The value of monitoring gabapentin blood concentrations has not been established.

6 ADVERSE REACTIONS

The following adverse reactions are described elsewhere in the labeling:

- Suicidal Behavior and Ideation [see Warnings and Precautions (5.1)]
- Increased Risk of Adverse Reactions with Abrupt or Rapid Discontinuation [see Warnings and Precautions (5.2)]
- Respiratory Depression [see Warnings and Precautions (5.3)]
- Tumorigenic Potential [see Warnings and Precautions (5.4)]
- Drug Reaction with Eosinophilia and Systemic Symptoms (DRESS)/Multiorgan Hypersensitivity [see Warnings and Precautions (5.5)]
- Laboratory Tests [see Warnings and Precautions (5.6)]

6.1 Clinical Trials Experience

Because clinical trials are conducted under widely varying conditions, adverse reaction rates observed in the clinical trials of a drug cannot be directly compared to rates in the clinical trials of another drug and may not reflect the rates observed in practice.

A total of 359 patients with neuropathic pain associated with postherpetic neuralgia have received GRALISE at doses up to 1,800 mg daily during placebo-controlled clinical studies. In clinical trials in patients with postherpetic neuralgia, 9.7% of the 359 patients treated with GRALISE and 6.9% of 364 patients treated with placebo discontinued prematurely due to adverse reactions. In the GRALISE treatment group, the most common reason for discontinuation due to adverse reactions was dizziness. Of GRALISE-treated patients who experienced adverse reactions in clinical studies, the majority of those adverse reactions were either "mild" or "moderate".

Table 4 lists all adverse reactions, regardless of causality, occurring in at least 1% of patients with neuropathic pain associated with postherpetic neuralgia in the GRALISE group for which the incidence was greater than in the placebo group.

Table 4: Treatment-Emergent Adverse Reaction Incidence in Controlled Trials in Neuropathic Pain Associated with Postherpetic Neuralgia (Events in at Least 1% of all GRALISE-Treated Patients and More Frequent Than in the Placebo Group)
Body System - Preferred Term | GRALISE N = 359 % | Placebo N = 364 %
Ear and Labyrinth Disorders
Vertigo | 1.4 | 0.5
Gastrointestinal Disorders
Diarrhea | 3.3 | 2.7
Dry mouth | 2.8 | 1.4
Constipation | 1.4 | 0.3
Dyspepsia | 1.4 | 0.8
General Disorders
Peripheral edema | 3.9 | 0.3
Pain | 1.1 | 0.5
Infections and Infestations
Nasopharyngitis | 2.5 | 2.2
Urinary tract infection | 1.7 | 0.5
Investigations
Weight increased | 1.9 | 0.5
Musculoskeletal and Connective Tissue Disorders
Pain in extremity | 1.9 | 0.5
Back pain | 1.7 | 1.1
Nervous System Disorders
Dizziness | 10.9 | 2.2
Somnolence | 4.5 | 2.7
Headache | 4.2 | 4.1
Lethargy | 1.1 | 0.3

In addition to the adverse reactions reported in Table 4 above, the following adverse reactions with an uncertain relationship to GRALISE were reported during the clinical development for the treatment of postherpetic neuralgia. Events in more than 1% of patients but equally or more frequently in the GRALISE-treated patients than in the placebo group included blood pressure increase, confusional state, gastroenteritis viral, herpes zoster, hypertension, joint swelling, memory impairment, nausea, pneumonia, pyrexia, rash, seasonal allergy, and upper respiratory infection.

6.2 Postmarketing and Other Experience with other Formulations of Gabapentin

In addition to the adverse experiences reported during clinical testing of gabapentin, the following adverse experiences have been reported in patients receiving other formulations of marketed gabapentin. These adverse experiences have not been listed above and data are insufficient to support an estimate of their incidence or to establish causation. The listing is alphabetized: angioedema, blood glucose fluctuation, breast enlargement, bullous pemphigoid, elevated creatine kinase, elevated liver function tests, erythema multiforme, fever, hyponatremia, jaundice, movement disorder, Stevens-Johnson syndrome.

There are postmarketing reports of withdrawal symptoms after discontinuation of gabapentin. Reported adverse reactions include, but are not limited to, seizures, depression, suicidal ideationand behavior, agitation, confusion, disorientation, psychotic symptoms, anxiety, insomnia, nausea, pain, sweating, tremor, headache, dizziness, and malaise [see Warnings and Precautions(5.2)].

There are postmarketing reports of life-threatening or fatal respiratory depression in patients taking gabapentin with opioids or other central nervous system (CNS) depressants, or in the setting of underlying respiratory impairment.

7 DRUG INTERACTIONS

In vitro studies were conducted to investigate the potential of gabapentin to inhibit the major cytochrome P450 enzymes (CYP1A2, CYP2A6, CYP2C9, CYP2C19, CYP2D6, CYP2E1, and CYP3A4) that mediate drug and xenobiotic metabolism using isoform selective marker substrates and human liver microsomal preparations. Only at the highest concentration tested (171 mcg/mL; 1mM) was a slight degree of inhibition (14% to 30%) of isoform CYP2A6 observed. No inhibition of any of the other isoforms tested was observed at gabapentin concentrations up to 171 mcg/mL (approximately 15 times the Cmax at 3,600 mg/day).

Gabapentin is not appreciably metabolized nor does it interfere with the metabolism of commonly coadministered antiepileptic drugs.

The drug interaction data described in this section were obtained from studies involving healthy adults and adult patients with epilepsy.

7.1 Phenytoin

In a single (400 mg) and multiple dose (400 mg three times daily) study of gabapentin immediate release in epileptic patients (N=8) maintained on phenytoin monotherapy for at least 2 months, gabapentin had no effect on the steady-state trough plasma concentrations of phenytoin and phenytoin had no effect on gabapentin pharmacokinetics.

7.2 Carbamazepine

Steady-state trough plasma carbamazepine and carbamazepine 10, 11 epoxide concentrations were not affected by concomitant gabapentin immediate release (400 mg three times daily; N=12) administration. Likewise, gabapentin pharmacokinetics were unaltered by carbamazepine administration.

7.3 Valproic Acid

The mean steady-state trough serum valproic acid concentrations prior to and during concomitant gabapentin immediate release administration (400 mg three times daily; N=17) were not different and neither were gabapentin pharmacokinetic parameters affected by valproic acid.

7.4 Phenobarbital

Estimates of steady-state pharmacokinetic parameters for phenobarbital or gabapentin immediate release (300 mg three times daily; N=12) are identical whether the drugs are administered alone or together.

7.5 Naproxen

Coadministration of single doses of naproxen (250 mg) and gabapentin immediate release (125 mg) to 18 volunteers increased gabapentin absorption by 12% to 15%. Gabapentin immediate release had no effect on naproxen pharmacokinetics. The doses are lower than the therapeutic doses for both drugs. The effect of coadministration of these drugs at therapeutic doses is not known.

7.6 Hydrocodone

Coadministration of gabapentin immediate release (125 mg and 500 mg) and hydrocodone (10 mg) reduced hydrocodone Cmax by 3% and 21%, respectively, and AUC by 4% and 22%, respectively. The mechanism of this interaction is unknown. Gabapentin AUC values were increased by 14%; the magnitude of the interaction at other doses is not known.

7.7 Morphine

When a single dose (60 mg) of controlled-release morphine capsule was administered 2 hours prior to a single dose (600 mg) of gabapentin immediate release in 12 volunteers, mean gabapentin AUC values increased by 44% compared to gabapentin immediate release administered without morphine. The pharmacokinetics of morphine were not affected by administration of gabapentin immediate release 2 hours after morphine. The magnitude of this interaction at other doses is not known.

7.8 Cimetidine

Cimetidine 300 mg decreased the apparent oral clearance of gabapentin by 14% and creatinine clearance by 10%. The effect of gabapentin immediate release on cimetidine was not evaluated. This decrease is not expected to be clinically significant.

7.9 Oral Contraceptives

Gabapentin immediate release (400 mg three times daily) had no effect on the pharmacokinetics of norethindrone (2.5 mg) or ethinyl estradiol (50 mcg) administered as a single tablet, except that the Cmax of norethindrone was increased by 13%. This interaction is not considered to be clinically significant.

7.10 Antacid (containing aluminum hydroxide and magnesium hydroxide)

An antacid containing aluminum hydroxide and magnesium hydroxide reduced the bioavailability of gabapentin immediate release by about approximately 20%, but by only 5% when gabapentin immediate release was taken 2 hours after the antacid. It is recommended that GRALISE be taken at least 2 hours following the antacid (containing aluminum hydroxide and magnesium hydroxide) administration.

7.11 Probenecid

Gabapentin immediate release pharmacokinetic parameters were comparable with and without probenecid, indicating that gabapentin does not undergo renal tubular secretion by the pathway that is blocked by probenecid.

7.12 Drug/Laboratory Test Interactions

False positive readings were reported with the Ames-N-Multistix SG® dipstick test for urine protein when gabapentin was added to other antiepileptic drugs; therefore, the more specific sulfosalicylic acid precipitation procedure is recommended to determine the presence of urine protein.

8 USE IN SPECIFIC POPULATIONS

8.1 Pregnancy

Pregnancy Exposure Registry

There is a pregnancy exposure registry that monitors pregnancy outcomes in women exposed to gabapentin, including GRALISE, during pregnancy. Encourage women who are taking GRALISE during pregnancy to enroll in the North American Antiepileptic Drug (NAAED) Pregnancy Registry by calling the toll free number 1-888-233-2334 or visiting https://www.aedpregnancyregistry.org/.

Risk Summary

Available data from published prospective and retrospective cohort studies, and case reports over decades of use with gabapentin during pregnancy have not identified a drug-associated risk of major birth defects. The available data are insufficient to evaluate a drug-associated risk of miscarriage and other maternal or fetal outcomes. In nonclinical studies in mice, rats, and rabbits, gabapentin was developmentally toxic (increased fetal skeletal and visceral abnormalities, and increased embryofetal mortality) when administered to pregnant animals at doses similar to those used clinically (see Data).

Postmarketing data suggest that extended gabapentin use with opioids close to delivery mayincrease the risk of neonatal withdrawal versus opioids alone [see Clinical Considerations]. Although there is at least one report of neonatal withdrawal syndrome in an infant exposed togabapentin alone during pregnancy, there are no comparative epidemiologic studies evaluatingthis association. Therefore, it is not known whether exposure to gabapentin alone late inpregnancy may cause withdrawal signs and symptoms.

The estimated background risk of major birth defects and miscarriage for the indicated populations is unknown. All pregnancies have a background risk of birth defect, loss, or other adverse outcomes. In the U.S. general population, the estimated background risk of major birth defects and miscarriage in clinically recognized pregnancies is 2% to 4% and 15% to 20%, respectively.

Clinical Considerations

Fetal/Neonatal Adverse Reactions

Neonatal withdrawal syndrome has been reported in newborns exposed to gabapentin in utero foran extended period of time when also exposed to opioids close to delivery. Neonatal withdrawal signs and symptoms reported have included tachypnea, vomiting, diarrhea, hypertonia, irritability, sneezing, poor feeding, hyperactivity, abnormal sleep pattern, and tremor. Reported signs and symptoms that may also be related to withdrawal include tongue thrusting, wandering eye movements while awake, back arching, and continuous extremity movements. Observe neonates exposed to GRALISE and opioids for signs and symptoms of neonatal withdrawal and manage accordingly.

Data

Animal Data

When pregnant mice received oral doses of gabapentin (1,000 or 3,000 mg/kg/day, approximately 3 to 8 times the maximum recommended dose of 1,800 mg on a mg/m^2 basis) during the period of organogenesis, embryofetal toxicity (increased incidences of skeletal variations) was observed. The no effect level was 500 mg/kg/day, representing approximately the maximum recommended human dose [MRHD] on a mg/m^2 basis.

When rats were dosed prior to and during mating, and throughout gestation, pups from all dose groups (500, 1,000 and 2,000 mg/kg/day) were affected. These doses are equivalent to approximately 3 to 11 times the MRHD on a mg/m^2 basis. There was an increased incidence of hydroureter and/or hydronephrosis in rats in a study of fertility and general reproductive performance at 2,000 mg/kg/day with no effect at 1,000 mg/kg/day, in a teratology study at 1,500 mg/kg/day with no effect at 300 mg/kg/day, and in a perinatal and postnatal study at all doses studied (500, 1,000 and 2,000 mg/kg/day). The doses at which the effects occurred are approximately 3 to 11 times the maximum recommended dose of 1,800 mg on a mg/m^2 basis; the no-effect doses were approximately 5 times (Fertility and General Reproductive Performance study) and approximately equal to (Teratogenicity study) the MRHD on a mg/m^2 basis. Other than hydroureter and hydronephrosis, the etiologies of which are unclear, the incidence of malformations was not increased compared to controls in offspring of mice, rats, or rabbits given doses up to 8 times (mice), 10 times (rats), or 16 times (rabbits) the human daily dose on a mg/m^2 basis.

When pregnant rabbits were treated with gabapentin during the period of organogenesis, an increase in embryofetal mortality was observed at 60, 300, and 1,500 mg/kg/day (0.6 to 16 times the MRHD on a mg/m^2 basis).

In a published study, gabapentin (400 mg/kg/day) was administered by intraperitoneal injection to neonatal mice during the first postnatal week, a period of synaptogenesis in rodents (corresponding to the last trimester of pregnancy in humans). Gabapentin caused a marked decrease in neuronal synapse formation in brains of intact mice and abnormal neuronal synapse formation in a mouse model of synaptic repair. Gabapentin has been shown in vitro to interfere with activity of the α2δ subunit of voltage-activated calcium channels, a receptor involved in neuronal synaptogenesis. The clinical significance of these findings is unknown.

8.2 Lactation

Risk Summary

Gabapentin is present in human milk following oral administration. Adverse effects on the breastfed infant have not been reported. There are no data on the effects of the drug on milk production. The developmental and health benefits of breastfeeding should be considered along with the mother's clinical need for GRALISE and any potential adverse effects on the breastfed infant from GRALISE or from the underlying maternal condition.

8.4 Pediatric Use

The safety and effectiveness of GRALISE in the management of postherpetic neuralgia in patients less than 18 years of age has not been studied.

8.5 Geriatric Use

The total number of patients treated with GRALISE in controlled clinical trials in patients with postherpetic neuralgia was 359, of which 63% were 65 years of age or older. The types and incidence of adverse events were similar across age groups except for peripheral edema, which tended to increase in incidence with age.

GRALISE is known to be substantially excreted by the kidney. Reductions in GRALISE dose should be made in patients with age-related compromised renal function [see Dosage and Administration (2.2)].

8.6 Hepatic Impairment

Because gabapentin is not metabolized, studies have not been conducted in patients with hepatic impairment.

8.7 Renal Impairment

GRALISE is known to be substantially excreted by the kidney. Dosage adjustment is necessary in patients with impaired renal function. GRALISE should not be administered in patients with CrCL between 15 and 30 or in patients undergoing hemodialysis [see Dosage and Administration (2.2)].

9 DRUG ABUSE AND DEPENDENCE

9.1 Controlled Substance

GRALISE contains gabapentin, which is not a controlled substance.

9.3 Dependence

Physical dependence is a state that develops as a result of physiological adaptation in response to repeated drug use, manifested by withdrawal signs and symptoms after abrupt discontinuation or a significant dose reduction of a drug.

After discontinuation of short-term and long-term treatment with gabapentin, withdrawal symptoms have been observed in some patients. Withdrawal symptoms may occur shortly after discontinuation, usually within 48 hours. In the postmarketing setting, reported adverse reactions have included, but not been limited to, seizures, depression, suicidal ideation and behavior,agitation, confusion, disorientation, psychotic symptoms, anxiety, insomnia, nausea, pain,sweating, tremor, headache, dizziness, and malaise. The abuse and dependence potential of GRALISE has not been evaluated in human studies.

10 OVERDOSAGE

Signs of acute toxicity in animals included ataxia, labored breathing, ptosis, sedation, hypoactivity, or excitation.

Acute oral overdoses of gabapentin have been reported. Symptoms include double-vision, tremor, slurred speech, drowsiness, altered mental status, dizziness, lethargy, and diarrhea. Fatal respiratory depression has been reported with gabapentin overdose, alone and in combination with other central nervous system (CNS) depressants.

Gabapentin can be removed by hemodialysis. Hemodialysis has been performed in overdose cases reported, and it may be indicated by the patient’s clinical state or in patients with significant renal impairment.

11 DESCRIPTION

GRALISE contains gabapentin, a gamma-aminobutyric acid (GABA) analogue, as the active pharmaceutical ingredient. Gabapentin's chemical name is 1-(aminomethyl)cyclohexaneacetic acid; with a molecular formula of C9H17NO2 and a molecular weight of 171.24 g/mol.

Gabapentin chemical structural formula is:

Gabapentin is a white to off-white crystalline solid with a pKa1 of 3.7 and a pKa2 of 10.7. It is freely soluble in water and acidic and basic solutions. The log of the partition coefficient (n-octanol/ 0.05M phosphate buffer) at pH 7.4 is -1.25.

GRALISE is intended for oral administration and is supplied as tablets containing 300 mg, 450 mg, 600 mg, 750 mg, or 900 mg of gabapentin USP.

Each 300 mg tablet contains the inactive ingredients Copovidone NF, Hypromellose USP, Magnesium Stearate NF, Microcrystalline Cellulose NF, Polyethylene Oxide NF, and white film coating (Polyvinyl Alcohol USP, Talc USP, Titanium Oxide USP, Polyethylene Glycol 3350 USP, and Lecithin NF (soya)).

Each 450 mg tablet contains the inactive ingredients Copovidone NF, Hypromellose USP, Magnesium Stearate NF, Polyethylene Oxide NF, and red film coating (Polyethylene glycol 3350 USP, Polyvinyl Alcohol USP, Talc USP, Titanium Oxide USP, and Iron Oxide Red NF).

Each 600 mg tablet contains the inactive ingredients Copovidone NF, Hypromellose USP, Magnesium Stearate NF, Polyethylene Oxide NF, and beige film coating (Polyethylene Glycol 3350 USP, Polyvinyl Alcohol USP, Talc USP, Titanium Oxide USP, Iron Oxide Yellow NF, and Iron Oxide Red NF).

Each 750 mg tablet contains the inactive ingredients Copovidone NF, Hypromellose USP, Magnesium Stearate NF, Polyethylene Oxide NF, and yellow film coating (Polyethylene Glycol 3350 USP, Polyvinyl Alcohol USP, Talc USP, Titanium oxide USP, and Iron Oxide Yellow NF).

Each 900 mg tablet contains the inactive ingredients Copovidone NF, Hypromellose USP, Magnesium Stearate NF, Polyethylene Oxide NF, and pink film coating (Polyethylene Glycol 3350 USP, Polyvinyl Alcohol USP, Talc USP, Titanium oxide USP, and Iron Oxide Red NF).

12 CLINICAL PHARMACOLOGY

12.1 Mechanism of Action

The mechanism of action by which gabapentin exerts its analgesic action is unknown but in animal models of analgesia, gabapentin prevents allodynia (pain-related behavior in response to a normally innocuous stimulus) and hyperalgesia (exaggerated response to painful stimuli). Gabapentin prevents pain-related responses in several models of neuropathic pain in rats and mice (e.g., spinal nerve ligation models, spinal cord injury model, acute herpes zoster infection model). Gabapentin also decreases pain-related responses after peripheral inflammation (carrageenan footpad test, late phase of formulin test), but does not alter immediate pain-related behaviors (rat tail flick test, formalin footpad acute phase). The relevance of these models to human pain is not known.

Gabapentin is structurally related to the neurotransmitter GABA (gamma-aminobutyric acid), but it does not modify GABAA or GABAB radioligand binding, it is not converted metabolically into GABA or a GABA agonist, and it is not an inhibitor of GABA uptake or degradation. In radioligand binding assays at concentrations up to 100 μM, gabapentin did not exhibit affinity for a number of other receptor sites, including benzodiazepine, glutamate, N-methyl-D-aspartate (NMDA), quisqualate, kainate, strychnine-insensitive or strychnine-sensitive glycine; alpha 1, alpha 2, or beta adrenergic; adenosine A1 or A2; cholinergic, muscarinic, or nicotinic; dopamine D1 or D2; histamine H1; serotonin S1 or S2; opiate mu, delta, or kappa; cannabinoid 1; voltage-sensitive calcium channel sites labeled with nitrendipine or diltiazem; or at voltage-sensitive sodium channel sites labeled with batrachotoxinin A20-alpha-benzoate. Gabapentin did not alter the cellular uptake of dopamine, noradrenaline, or serotonin.

In vitro studies with radiolabeled gabapentin have revealed a gabapentin binding site in areas of rat brain including neocortex and hippocampus. A high-affinity binding protein in animal brain tissue has been identified as an auxiliary subunit of voltage-activated calcium channels. However, functional correlates of gabapentin binding, if any, remain to be elucidated. It is hypothesized that gabapentin antagonizes thrombospondin binding to α2δ-1 as a receptor involved in excitatory synapse formation and suggested that gabapentin may function therapeutically by blocking new synapse formation.

12.2 Pharmacodynamics

No pharmacodynamic studies have been conducted with GRALISE.

12.3 Pharmacokinetics

Absorption

Gabapentin is absorbed from the proximal small bowel by a saturable L-amino transport system. Gabapentin bioavailability is not dose proportional; as the dose is increased, bioavailability decreases.

When GRALISE (1,800 mg once daily) and gabapentin immediate release (600 mg three times a day) were administered with high fat meals (50% of calories from fat), GRALISE has a higher Cmax and lower AUC at steady state compared to gabapentin immediate release (Table 5). Time to reach maximum plasma concentration (Tmax) for GRALISE is 8 hours, which is about 4-6 hours longer compared to gabapentin immediate release.

Table 5: Mean ± SD Steady-State Pharmacokinetics for GRALISE and Gabapentin Immediate Release in Healthy Subjects under high-fat high calorie fed state (Day 5, n = 21)
Pharmacokinetic Parameter (Mean ± SD) | GRALISE 1,800 mg QD (3 x 600 mg) | Gabapentin Immediate Release 600 mg TID
AUC0-24 (μg.hr/mL) | 132.8 ± 34.7 | 141.3 ± 29.8
Cmax (μg/mL) | 9.59 ± 2.33 | 8.54 ± 1.72
Cmin (μg/mL) | 1.84 ± 0.65 | 2.6 ± 0.78
Tmax (hr)$ | 8 (3-12) | 2 (1-5)*
$Tmax is presented as median (range); * relative to most recent dose

The single dose pharmacokinetic parameters of 900 mg strength under high fat-high calorie fed state and low fat-low calorie fed state are presented shown in Table 6.

Table 6: Mean ± SD Single-Dose Pharmacokinetic parameters for GRALISE 900 mg strength in Healthy Subjects (n = 27)
Pharmacokinetic Parameter (Mean ± SD) | GRALISE 1,800 mg (2 x 900 mg tablets)
Pharmacokinetic Parameter (Mean ± SD) | High fat- high calorie fed state | Low fat- low calorie fed state
Cmax (μg/mL) | 9.49 ± 1.93 | 6.50 ± 2.16
AUCt (μg.hr/mL) | 127.2 ± 42.8 | 79.1 ± 39.4
AUCinf (μg.hr/mL) | 133.2 ± 43.2 | 84.8 ± 39.4
Tmax (hr)$ | 7 (4-12) | 4 (3-12)
$Tmax is presented as median (range)

Do not use GRALISE as a substitute for other gabapentin products because of differing pharmacokinetic profiles that affect frequency of administration.

GRALISE should be taken with evening meals. If it is taken on an empty stomach, the bioavailability will be substantially lower.

Administration of GRALISE with food increases the rate and extent of absorption of gabapentin compared to the fasted state. Cmax of gabapentin increases 33-84% and AUC of gabapentin increases 33-118% with food depending on the fat content of the meal. GRALISE should be taken with food.

Distribution

Gabapentin is less than 3% bound to plasma proteins. After 150 mg intravenous administration, the mean ± SD volume of distribution is 58 ± 6 L.

Elimination

Gabapentin is eliminated by renal excretion as unchanged drug.

In patients with normal renal function given gabapentin immediate release 1,200 to 3,000 mg/day, the drug elimination half-life (t1/2) was 5 to 7 hours. Elimination kinetics do not change with dose level or multiple doses.

Metabolism

Gabapentin is not appreciably metabolized in humans.

Excretion

Gabapentin elimination rate constant, plasma clearance, and renal clearance are directly proportional to creatinine clearance. In elderly patients and patients with impaired renal function, plasma clearance is reduced. Gabapentin can be removed from plasma by hemodialysis.

Dosage adjustment in patients with compromised renal function is necessary. In patients undergoing hemodialysis, GRALISE should not be administered [see Dosage and Administration (2.2)].

12.4 Special Populations

Renal Insufficiency: As renal function decreases, renal and plasma clearances and the apparent elimination rate constant decrease, while Cmax and t1/2 increase.

In patients (N=60) with creatinine clearance of at least 60, 30 to 59, or less than 30 mL/min, the median renal clearance rates for a 400 mg single dose of gabapentin immediate release were 79, 36, and 11 mL/min, respectively, and the median t1/2 values were 9.2, 14, and 40 hours, respectively.

Dosage adjustment is necessary in patients with impaired renal function [see Dosage and Administration (2.2)].

Hemodialysis: In a study in anuric adult subjects (N=11), the apparent elimination half-life of gabapentin on nondialysis days was about 132 hours; during dialysis the apparent half-life of gabapentin was reduced to 3.8 hours. Hemodialysis thus has a significant effect on gabapentin elimination in anuric subjects. GRALISE should not be administered in patients undergoing hemodialysis. Alternative formulations of gabapentin products should be considered in patients undergoing hemodialysis.

Elderly: Apparent oral and renal clearances of gabapentin decrease with increasing age, although this may be related to the decline in renal function with age. Reductions in gabapentin dose should be made in patients with age-related compromised renal function [see Dosage and Administration (2.2)].

Hepatic Impairment: Because gabapentin is not metabolized, studies have not been conducted in patients with hepatic impairment.

Pediatrics: The pharmacokinetics of GRALISE have not been studied in patients less than 18 years of age.

Gender: Although no formal study has been conducted to compare the pharmacokinetics of gabapentin in men and women, it appears that the pharmacokinetic parameters for males and females are similar and there are no significant gender differences.

Race: Pharmacokinetic differences due to race have not been studied. Because gabapentin is primarily renally excreted and there are no important racial differences in creatinine clearance, pharmacokinetic differences due to race are not expected.

13 NONCLINICAL TOXICOLOGY

13.1 Carcinogenesis, Mutagenesis, Impairment of Fertility

Carcinogenesis

Gabapentin was given in the diet to mice at 200, 600, and 2,000 mg/kg/day and to rats at 250, 1,000, and 2,000 mg/kg/day for 2 years. A statistically significant increase in the incidence of pancreatic acinar cell adenoma and carcinomas was found in male rats receiving the high dose; the no-effect dose for the occurrence of carcinomas was 1,000 mg/kg/day. Peak plasma concentrations of gabapentin in rats receiving the high dose of 2,000 mg/kg/day were more than 10 times higher than plasma concentrations in humans receiving 1,800 mg per day and in rats receiving 1,000 mg/kg/day peak plasma concentrations were more than 6.5 times higher than in humans receiving 1,800 mg/day. The pancreatic acinar cell carcinomas did not affect survival, did not metastasize and were not locally invasive. The relevance of this finding to carcinogenic risk in humans is unclear.

Studies designed to investigate the mechanism of gabapentin-induced pancreatic carcinogenesis in rats indicate that gabapentin stimulates DNA synthesis in rat pancreatic acinar cells in vitro and, thus, may be acting as a tumor promoter by enhancing mitogenic activity. It is not known whether gabapentin has the ability to increase cell proliferation in other cell types or in other species, including humans.

Mutagenesis

Gabapentin did not demonstrate mutagenic or genotoxic potential in 3 in vitro and 4 in vivo assays. It was negative in the Ames test and the in vitro HGPRT forward mutation assay in Chinese hamster lung cells; it did not produce significant increases in chromosomal aberrations in the in vitro Chinese hamster lung cell assay; it was negative in the in vivo chromosomal aberration assay and in the in vivo micronucleus test in Chinese hamster bone marrow; it was negative in the in vivo mouse micronucleus assay; and it did not induce unscheduled DNA synthesis in hepatocytes from rats given gabapentin.

Impairment of Fertility

No adverse effects on fertility or reproduction were observed in rats at doses up to 2,000 mg/kg (approximately 11 times the maximum recommended human dose on an mg/m^2 basis).

14 CLINICAL STUDIES

The efficacy of GRALISE for the management of postherpetic neuralgia was established in a double-blind, placebo-controlled, multicenter study. This study enrolled patients between the age of 21 to 89 with postherpetic neuralgia persisting for at least 6 months following healing of herpes zoster rash and a minimum baseline pain intensity score of at least 4 on an 11-point numerical pain rating scale ranging from 0 (no pain) to 10 (worst possible pain).

This 11-week study compared GRALISE 1,800 mg once daily with placebo. A total of 221 and 231 patients were treated with GRALISE or placebo, respectively. The study treatment including titration for all patients comprised a 10-week treatment period followed by 1-week of dose tapering. Double-blind treatment began with titration starting at 300 mg/day and titrated up to a total daily dose of 1,800 mg over 2 weeks, followed by 8 weeks fixed dosing at 1,800 mg once daily, and then 1 week of dose tapering. During the 8-week stable dosing period, patients took 3 active or placebo tablets each night with the evening meal. During baseline and treatment, patients recorded their pain in a daily diary using an 11-point numeric pain rating scale. The mean baseline pain score was 6.6 and 6.5 for GRALISE and placebo-treated patients, respectively.

Treatment with GRALISE statistically significantly improved the endpoint mean pain score from baseline. For various degrees of improvement in pain from baseline to study endpoint, Figure 1 shows the fraction of patients achieving that degree of improvement. The figure is cumulative, so that patients whose change from baseline is, for example, 50%, are also included at every level of improvement below 50%. Patients who did not complete the study were assigned 0% improvement.

16 HOW SUPPLIED/STORAGE AND HANDLING

GRALISE (gabapentin) Tablets are supplied as follows:

• 300 mg tablets:
GRALISE 300 mg tablets are white, oval, debossed with “SLV” on one side and “300” on the other side.
NDC 52427-803-90 (Bottle of 90)

• 450 mg tablets:
GRALISE 450 mg tablets are red, oval, debossed with “ALM” on one side and “450” on the other side.
NDC 52427-804-60 (Bottle of 60)

• 600 mg tablets:
GRALISE 600 mg tablets are beige, oval, debossed with “SLV” on one side and “600” on the other side.
NDC 52427-806-90 (Bottle of 90)

• 750 mg tablets:
GRALISE 750 mg tablets are yellow, oval, debossed with “ALM” on one side and “750” on the other side.
NDC 52427-850-60 (Bottle of 60)

• 900 mg tablets:
GRALISE 900 mg tablets are pink, oval, debossed with “ALM” on one side and “900” on
NDC 52427-890-60 (Bottle of 60)

Storage

Store at 20ºC to 25ºC (68ºF to 77ºF); excursions permitted to 15ºC to 30ºC (59ºF to 86ºF) [see USP Controlled Room Temperature].

Keep out of reach of children.

17 PATIENT COUNSELING INFORMATION

Advise patients of the availability of a Medication Guide, and instruct them to read the Medication Guide prior to taking GRALISE.

- Advise patients that GRALISE is not substitutable with other formulations of gabapentin.
- Advise patients to take GRALISE only as prescribed. GRALISE may cause dizziness, somnolence, and other signs and symptoms of CNS depression.
- Advise patients not to drive or operate other complex machinery until they have gained sufficient experience on GRALISE to gauge whether or not it adversely affects their mental and/or motor performance. Advise patients who require concomitant treatment with morphine to tell their prescriber if they develop signs of CNS depression such as somnolence. If this occurs the dose of GRALISE or morphine should be reduced accordingly.
- Advise patients that if they miss a dose of GRALISE to take it with food as soon as they remember. If it is almost time for the next dose, just skip the missed dose and take the next dose at the regular time. Do not take two doses at the same time.
- Advise patients that if they take too much GRALISE, to call their healthcare provider or poison control center, or go to the nearest emergency room right away.

Suicidal Thoughts and Behavior

Counsel patients, their caregivers, and families that AEDs, including gabapentin, the active ingredient in GRALISE, may increase the risk of suicidal thoughts and behavior and of the need to be alert for the emergence or worsening of symptoms of depression, any unusual changes in mood or behavior, or the emergence of suicidal thoughts, behavior, or thoughts about self-harm. Instruct patients, caregivers, and families to report behaviors of concern immediately to healthcare providers. Also inform patients who plan to or have discontinued GRALISE that suicidal thoughts and behavior can appear even after the drug is stopped [see Warnings and Precautions (5.1)].

Respiratory Depression

Inform patients about the risk of respiratory depression. Include information that the risk is greatest for those using concomitant central nervous system (CNS) depressants (such as opioid analgesics) or in those with underlying respiratory impairment. Teach patients how to recognize respiratory depression and advise them to seek medical attention immediately if it occurs [see Warnings and Precautions (5.3)].

Dosing and Administration

GRALISE is not substitutable with other gabapentin products because of differing pharmacokinetic profiles that affect the frequency of administration.

The safety and effectiveness of GRALISE in patients with epilepsy has not been studied.

Advise patients that GRALISE should be taken orally once daily with the evening meal. GRALISE tablets should be swallowed whole. Do not split, crush, or chew the tablets [see Dosage and Administration (2.1)].

Use in Pregnancy

Advise patients to notify their healthcare provider if they become pregnant or intend to become pregnant during treatment with GRALISE, and to notify their physician if they are breast feeding or intend to breast feed during therapy [see Use in Specific Populations (8.1) and (8.2)].

Encourage patients to enroll in the North American Antiepileptic Drug (NAAED) PregnancyRegistry if they become pregnant. This registry is collecting information about the safety ofantiepileptic drugs during pregnancy. To enroll, patients can call the toll-free number 1-888-233-2334 [see Use in Specific Populations (8.1)].

Distributed by:
Almatica Pharma LLC
Morristown, NJ 07960 USA

Brands listed are trademarks of their respective owners.

PI803-03

MEDICATION GUIDE

GRALISE® (gra leez')
(gabapentin) Tablets

Read this Medication Guide before you start taking GRALISE and each time you get a refill. There may be new information. This information does not take the place of talking to your healthcare provider about your medical condition or treatment. If you have any questions about GRALISE, ask your healthcare provider or pharmacist.

What is the most important information I should know about GRALISE?

Do not stop taking GRALISE without first talking with your healthcare provider. Stopping GRALISE suddenly can cause serious problems.

Like other antiepileptic drugs, gabapentin, the active ingredient in GRALISE, may cause suicidal thoughts or actions in a very small number of people, about 1 in 500. This can happen while you take GRALISE or after stopping. However, it is not known if GRALISE is safe and effective in people with seizure problems (epilepsy). Therefore, GRALISE should not be used in place of other gabapentin products.

Call a healthcare provider right away if you have any of these symptoms, especially if they are new, worse, or worry you:

- thoughts about suicide or dying
- attempts to commit suicide
- serious breathing problems
- new or worse depression
- new or worse anxiety
- feeling agitated or restless
- panic attacks
- trouble sleeping (insomnia)
- new or worse irritability
- acting aggressive, being angry, or violent
- acting on dangerous impulses
- an extreme increase in activity and talking (mania)
- other unusual changes in behavior or mood

How can I watch for early symptoms of suicidal thoughts and actions?

- Pay attention to any changes, especially sudden changes, in mood, behaviors, thoughts, or feelings.
- Keep all follow-up visits with your healthcare provider as scheduled.
- Call your healthcare provider between visits as needed, especially if you are worried about symptoms.

Serious breathing problems

- Serious breathing problems can occur when GRALISE is taken with other medicines that can cause severe sleepiness or decreased awareness, or when it is taken by someone who already has breathing problems. Watch for increased sleepiness or decreased breathing when starting GRALISE or when the dose is increased. Get help right away if breathing problems occur.

Do not stop taking GRALISE without first talking with your healthcare provider.

- Stopping GRALISE suddenly can cause serious problems.

What is GRALISE?

GRALISE is a prescription medicine used in adults, 18 years and older, to treat:

- pain from damaged nerves (neuropathic pain) that follows healing of shingles (a painful rash that comes after a herpes zoster infection).

It is not known if GRALISE is safe and effective in people with seizure problems (epilepsy).

It is not known if GRALISE is safe and effective in children under 18 years of age with postherpetic pain.

GRALISE is not substitutable with other gabapentin products.

Who should not take GRALISE?

Do not take GRALISE if you are allergic to gabapentin or any of the ingredients in GRALISE. See the end of this Medication Guide for a complete list of ingredients in GRALISE.

What should I tell my healthcare provider before taking GRALISE?

Before taking GRALISE, tell your healthcare provider if you:

- have or have had depression, mood problems or suicidal thoughts or behavior
- have breathing problems
- have seizures
- have kidney problems or get kidney dialysis
- are pregnant or plan to become pregnant. It is not known if GRALISE can harm your unborn baby. Tell your healthcare provider right away if you become pregnant while taking GRALISE. You and your healthcare provider will decide if you should take GRALISE while you are pregnant.
  - If you become pregnant while taking GRALISE, talk to your healthcare provider about registering with the North American Antiepileptic Drug (NAAED) Pregnancy Registry. The purpose of this registry is to collect information about the safety of antiepileptic drugs, including gabapentin, the active ingredient in GRALISE, during pregnancy. You can enroll in this registry by calling 1-888-233-2334.
- are breastfeeding or plan to breastfeed. Gabapentin passes into your breast milk. Talk to your healthcare provider about the best way to feed your baby during treatment with GRALISE.

Tell your healthcare provider about all the medicines you take including prescription and non-prescription medicines, vitamins or herbal supplements. Especially tell your healthcare provider if you take any opioid pain medicine (such as oxycodone), or medicines for anxiety (such as lorazepam) or insomnia (such as zolpidem). You may have a higher chance for dizziness, sleepiness, or serious breathing problems if these medicines are taken with GRALISE.

Taking GRALISE with certain other medicines can cause side effects or affect how well they work. Do not start or stop other medicines without talking to your healthcare provider.

Know the medicines you take. Keep a list of them and show it to your healthcare provider and pharmacist when you get a new medicine.

How should I take GRALISE?

- Take GRALISE exactly as prescribed. Your healthcare provider will tell you how much GRALISE to take and when to take it. Take GRALISE at the same time each day.
- Do not change your dose or stop taking GRALISE without talking with your healthcare provider. If you stop taking GRALISE suddenly, you may experience side effects. Talk with your healthcare provider about how to stop GRALISE slowly.
- Take GRALISE with food one time each day with your evening meal.
- Take GRALISE tablets whole. Do not split, crush, or chew GRALISE tablets before swallowing.
- Your healthcare provider may change your dose of GRALISE. Do not change your dose of GRALISE without talking to your healthcare provider.
- If you miss a dose, take it as soon as you remember with food. If it is almost time for your next dose, just skip the missed dose. Take the next dose at your regular time. Do not take two doses at the same time.
- If you take too much GRALISE, call your healthcare provider or poison control center, or go to the nearest emergency room right away.
- If you are taking an antacid containing aluminum hydroxide and magnesium hydroxide, it is recommended that GRALISE be taken at least 2 hours following administration of the antacid.

What should I avoid while taking GRALISE?

- Do not drink alcohol or take other medicines that make you sleepy or dizzy while taking GRALISE without first talking to your healthcare provider. Taking GRALISE with alcohol or medicines that cause sleepiness or dizziness may make your sleepiness or dizziness worse.
- Do not operate heavy machines or do other dangerous activities until you know how GRALISE affects you. GRALISE can slow your thinking and motor skills.

What are the possible side effects of GRALISE?

The most common side effect of GRALISE is:

- dizziness

Tell your healthcare provider about any side effect that bothers you or that does not go away.

These are not all the possible side effects of GRALISE. For more information, ask your healthcare provider or pharmacist.

Call your doctor for medical advice about side effects. You may report side effects to FDA at 1-800-FDA-1088.

How should I store GRALISE?

Store GRALISE at 59°F to 86°F (15°C to 30°C)

- Keep GRALISE and all medicines out of the reach of children.

General information about the safe and effective use of GRALISE

Medicines are sometimes prescribed for purposes other than those listed in a Medication Guide. Do not use GRALISE for a condition for which it was not prescribed. Do not give GRALISE to other people, even if they have the same symptoms you have. It may harm them.

This Medication Guide summarizes the most important information about GRALISE. If you would like more information, talk with your healthcare provider. You can ask your healthcare provider or pharmacist for information about GRALISE that is written for health professionals.

For more information about GRALISE, call 1-877-447-7979.

What are the ingredients in GRALISE?

Active ingredient: gabapentin

Inactive ingredients:

300 mg tablet: copovidone, hypromellose, magnesium stearate, microcrystalline cellulose, polyethylene oxide, and white film coating (polyvinyl alcohol, titanium dioxide, talc, polyethylene glycol 3350, and lecithin (soya)).

450 mg tablet: copovidone, hypromellose, magnesium stearate, polyethylene oxide, and red film coating (polyethylene glycol, polyvinyl alcohol, talc, titanium dioxide, and iron oxide red).

600 mg tablet: copovidone, hypromellose, magnesium stearate, polyethylene oxide, and beige film coating (polyvinyl alcohol, titanium dioxide, talc, polyethylene glycol 3350, iron oxide yellow, and iron oxide red).

750 mg tablet: copovidone, hypromellose, magnesium stearate, polyethylene oxide, and yellow film coating (polyethylene glycol, polyvinyl alcohol, talc, titanium dioxide, and iron oxide yellow).

900 mg tablet: copovidone, hypromellose, magnesium stearate, polyethylene oxide, and pink film coating (polyethylene glycol, polyvinyl alcohol, talc, titanium dioxide, and iron oxide red).

Distributed by:
Almatica Pharma LLC
Morristown, NJ 07960 USA

Brands listed are trademarks of their respective owners.

PL803-02
Revised: 05/2025

This Medication Guide has been approved by the U.S. Food and Drug Administration.

PACKAGE LABEL

NDC 52427-803-90

ONCE-DAILY
Gralise®
(gabapentin) tablets

300 mg

Do not use Gralise as a substitute for other gabapentin products.

PHARMACIST: Dispense the accompanying Medication Guide to each patient.

PACKAGE LABEL

NDC 52427-804-60

ONCE-DAILY
Gralise®
(gabapentin) tablets

450 mg

Do not use Gralise as a substitute for other gabapentin products.

PHARMACIST: Dispense the accompanying Medication Guide to each patient.

PACKAGE LABEL

NDC 52427-806-90

ONCE-DAILY
Gralise®
(gabapentin) tablets

600 mg

Do not use Gralise as a substitute for other gabapentin products.

PHARMACIST: Dispense the accompanying Medication Guide to each patient.

PACKAGE LABEL

NDC 52427-850-60

ONCE-DAILY
Gralise®
(gabapentin) tablets

750 mg

Do not use Gralise as a substitute for other gabapentin products.

PHARMACIST: Dispense the accompanying Medication Guide to each patient.

PACKAGE LABEL

NDC 52427-890-60

ONCE-DAILY
Gralise®
(gabapentin) tablets

900 mg

Do not use Gralise as a substitute for other gabapentin products.

PHARMACIST: Dispense the accompanying Medication Guide to each patient.

PACKAGE LABEL

Professional Sample